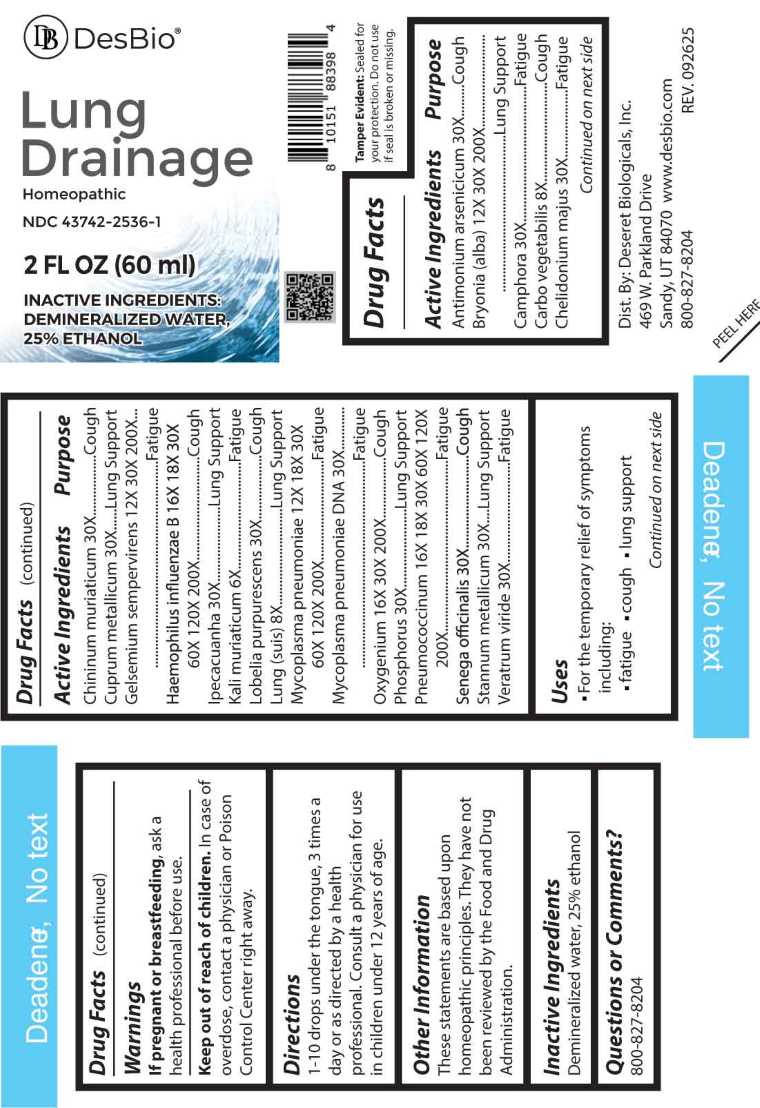 DRUG LABEL: Lung Drainage
NDC: 43742-2536 | Form: LIQUID
Manufacturer: Deseret Biologicals, Inc.
Category: homeopathic | Type: HUMAN OTC DRUG LABEL
Date: 20260105

ACTIVE INGREDIENTS: ANTIMONY ARSENATE 30 [hp_X]/1 mL; BRYONIA ALBA ROOT 12 [hp_X]/1 mL; CAMPHOR (NATURAL) 30 [hp_X]/1 mL; ACTIVATED CHARCOAL 8 [hp_X]/1 mL; CHELIDONIUM MAJUS WHOLE 30 [hp_X]/1 mL; QUININE HYDROCHLORIDE 30 [hp_X]/1 mL; COPPER 30 [hp_X]/1 mL; GELSEMIUM SEMPERVIRENS ROOT 12 [hp_X]/1 mL; HAEMOPHILUS INFLUENZAE TYPE B 16 [hp_X]/1 mL; IPECAC 30 [hp_X]/1 mL; POTASSIUM CHLORIDE 6 [hp_X]/1 mL; PRATIA PURPURASCENS 30 [hp_X]/1 mL; SUS SCROFA LUNG 8 [hp_X]/1 mL; MYCOPLASMA PNEUMONIAE 12 [hp_X]/1 mL; MYCOPLASMA PNEUMONIAE DNA 30 [hp_X]/1 mL; OXYGEN 16 [hp_X]/1 mL; PHOSPHORUS 30 [hp_X]/1 mL; STREPTOCOCCUS PNEUMONIAE 16 [hp_X]/1 mL; POLYGALA SENEGA ROOT 30 [hp_X]/1 mL; TIN 30 [hp_X]/1 mL; VERATRUM VIRIDE ROOT 30 [hp_X]/1 mL
INACTIVE INGREDIENTS: WATER; ALCOHOL

DRUG FACTS:

ACTIVE INGREDIENTS:

Antimonium Arsenicicum 30X, Bryonia (Alba) 12X, 30X, 200X, Camphora 30X, Carbo Vegetabilis 8X, Chelidonium Majus 30X, Chininum Muriaticum 30X, Cuprum Metallicum 30X, Gelsemium Sempervirens 12X, 30X, 200X, Haemophilus Influenzae B – 16X, 18X, 30X, 60X, 120X, 200X, Ipecacuanha 30X, Kali Muriaticum 6X, Lobelia Purpurescens 30X, Lung (Suis) 8X, Mycoplasma Pneumoniae 12X, 18X, 30X, 60X, 120X, 200X, Mycoplasma Pneumoniae DNA 30X, Oxygenium 16X, 30X, 200X, Phosphorus 30X, Pneumococcinum 16X, 18X, 30X, 60X, 120X, 200X, Senega Officinalis 30X, Stannum Metallicum 30X, Veratrum Viride 30X.

PURPOSE:

Antimonium Arsenicicum - Cough, Bryonia (Alba) – Lung Support, Camphora - Fatigue, Carbo Vegetabilis - Cough, Chelidonium Majus - Fatigue, Chininum Muriaticum - Cough, Cuprum Metallicum – Lung Support, Gelsemium Sempervirens - Fatigue, Haemophilus Influenzae B - Cough, Ipecacuanha – Lung Support, Kali Muriaticum - Fatigue, Lobelia Purpurescens - Cough, Lung (Suis) – Lung Support, Mycoplasma Pneumoniae - Fatigue, Mycoplasma Pneumoniae DNA - Fatigue, Oxygenium - Cough, Phosphorus – Lung Support, Pneumococcinum - Fatigue, Senega Officinalis - Cough, Stannum Metallicum – Lung Support, Veratrum Viride - Fatigue

USES:

• For the temporary relief of symptoms including:

• fatigue • cough • lung support

These statements are based upon homeopathic principles. They have not been reviewed by the Food and Drug Administration.

WARNINGS:

If pregnant or breastfeeding, ask a health professional before use.

Keep out of reach of children. In case of overdose, contact a physician or Poison Control Center right away.

Tamper Evident: Sealed for your protection. Do not use if seal is broken or missing.

KEEP OUT OF REACH OF CHILDREN:

In case of overdose, contact physician or a Poison Control Center right away.

DIRECTIONS:

1-10 drops under the tongue, 3 times a day or as directed by a health professional. Consult a physician for use in children under 12 years of age.

INACTIVE INGREDIENTS:

Demineralized water, 25% ethanol

QUESTIONS:

Dist. By: Deseret Biologicals, Inc.
469 W. Parkland Drive
Sandy, UT 84070

www.desbio.com

800-827-8204

PACKAGE LABEL DISPLAY:

DesBio
Lung Drainage
Homeopathic
NDC 43742-2536-1
2 FL OZ (60 ml)